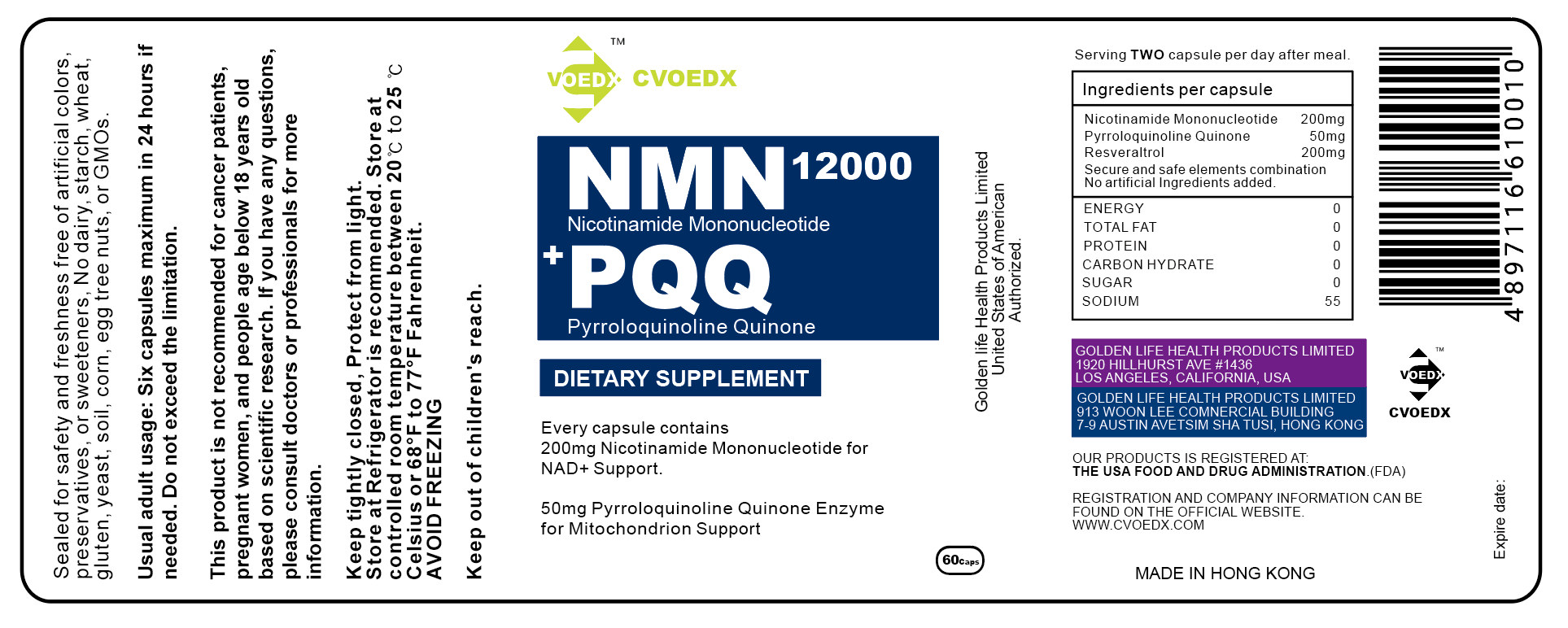 DRUG LABEL: NMNPQQ
NDC: 11777-001 | Form: POWDER
Manufacturer: Golden Life Health Products Limited
Category: otc | Type: HUMAN OTC DRUG LABEL
Date: 20201223

ACTIVE INGREDIENTS: PYRROLOQUINOLINEDIONE TRICARBOXYLIC ACID 10 mg/100 mg; NICOTINAMIDE RIBOTIDE 45 mg/100 mg
INACTIVE INGREDIENTS: RESVERATROL

DOSAGE AND ADMINISTRATION

serving Two capsule per day after meal.
Usual adult usage: Six capsules maximum in 24 hours ifneeded. Do not exceed the limitation.

information

Keep tightly closed, Protect from light.
Store at Refrigerator is recommended. Store at controlled room temperature between 20℃ to 25 ℃ celsius or 68°F to 77°F Fahrenheit

INDICATIONS AND USAGE

This product is not recommended for cancer patients,pregnant women, and people age below 18 years oldbased on scientific research. lf you have any questions,please consult doctors or professionals for more information.

INACTIVE INGREDIENT

Resveraltrol

ACTIVE INGREDIENT

Nicotinamide mononucleotide 200mg 45%

pyrroloquinoline quinone 50mg 10%

Keep out of children's reach.

PURPOSE

Every capsule contains
200mg Nicotinamide Mononucleotide for NAD+ Support.
50mg Pyrroloquinoline Quinone Enzymefor Mitochondrion Support

WARNINGS

Sealed for safety and freshness free of artificial colors,preservatives , or sweeteners, No dairy, starch, wheat,gluten, yeast, soil, corn, egg tree nuts, or GMOs.